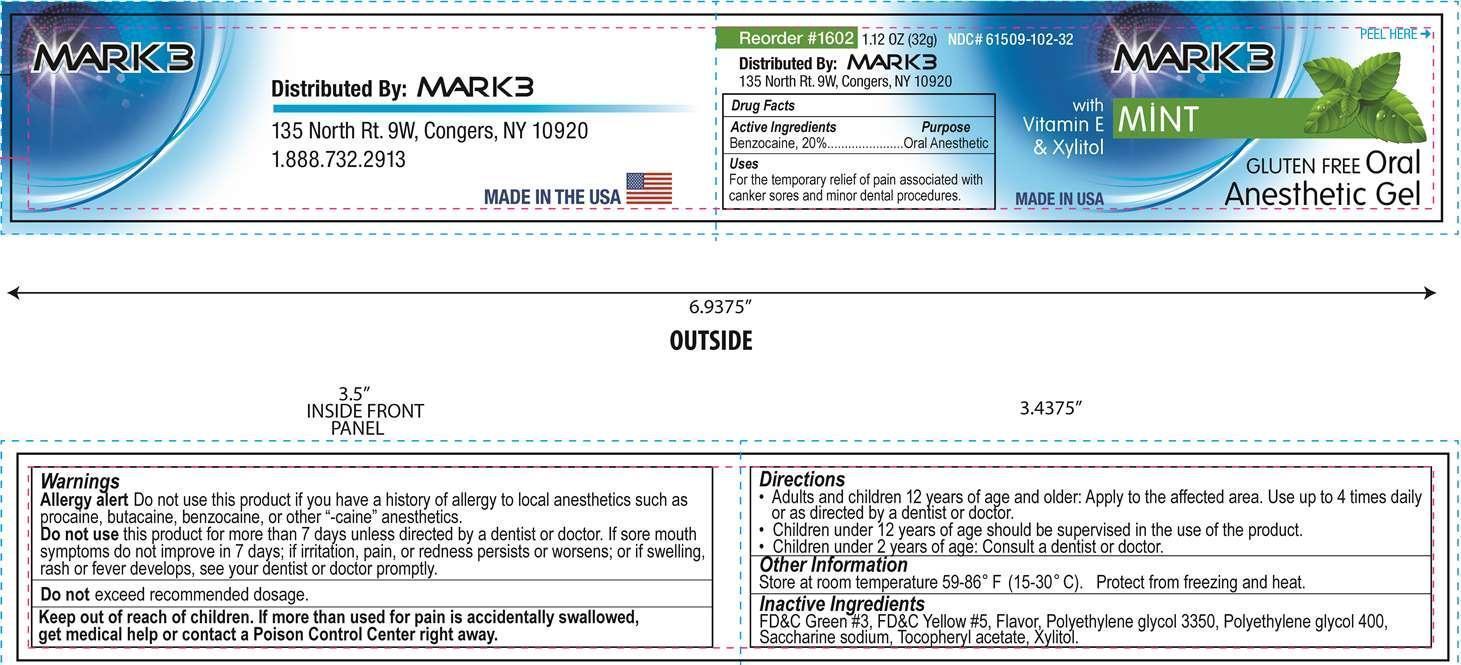 DRUG LABEL: Mark 3
NDC: 61509-102 | Form: GEL
Manufacturer: Cargus International, Inc.
Category: otc | Type: HUMAN OTC DRUG LABEL
Date: 20210323

ACTIVE INGREDIENTS: BENZOCAINE 6.4 g/32 g
INACTIVE INGREDIENTS: FD&C GREEN NO. 3; FD&C YELLOW NO. 5; POLYETHYLENE GLYCOL 3350; POLYETHYLENE GLYCOL 400; SACCHARIN SODIUM; .ALPHA.-TOCOPHEROL ACETATE; XYLITOL

Active Ingredient

Benzocaine, 20%

Purpose

Oral Anesthetic

Uses

For the temporary relief of pain associated with canker sores and minor dental procedures.

Warnings

Allergy alert Do not use this product if you have a history of allergy to local anesthetics such as procaine, butacaine, benzocaine, or other "-caine" anesthetics.

Do not

use this product for more than 7 days unless directed by a dentist or doctor. If sore mouth symptoms do not improve in 7 days; if irritation, pain, or redness persists or worsens; or if swelling, rash or fever develops, see your dentist or doctor promptly.

Do not

exceed recommended dosage.

Keep out of reach of children.

If more than used for pain is accidentially swallowed, get medical help or contact a Poison Control Center right away.

Directions

- Adults and children 12 years of age and older: Apply to the affected area. Use up to 4 times daily or as directed by a dentist or doctor
- Children under 12 years of age should be supervised in the use of the product.
- Children under 2 years of age: Consult a dentist or doctor.

Other Information

Store at room temperature 59 - 86°F (15 - 30°C). Protect from freezing and heat.

Inactive Ingredients

FD&C Green No. 3, FD&C Yellow No. 5, Flavor, Polyethylene glycol 3350, Polyethylene glycol 400, Saccharine sodium, Tocopheryl acetate, Xylitol

Distributed by

Mark 3, 135 North Rt. 9W, Congers, NY 10920

1.888.732.2913

PACKAGE LABEL

Mark 3

Oral Anesthetic Gel

Mint

Gluten Free

with Vitamin E and Xylitol

NDC 61509-102-32

Net Wt. 1.12 oz. (32 g)

Distributed by Mark 3, 135 North Rt. 9W, Congers, NY 10920

Made in USA